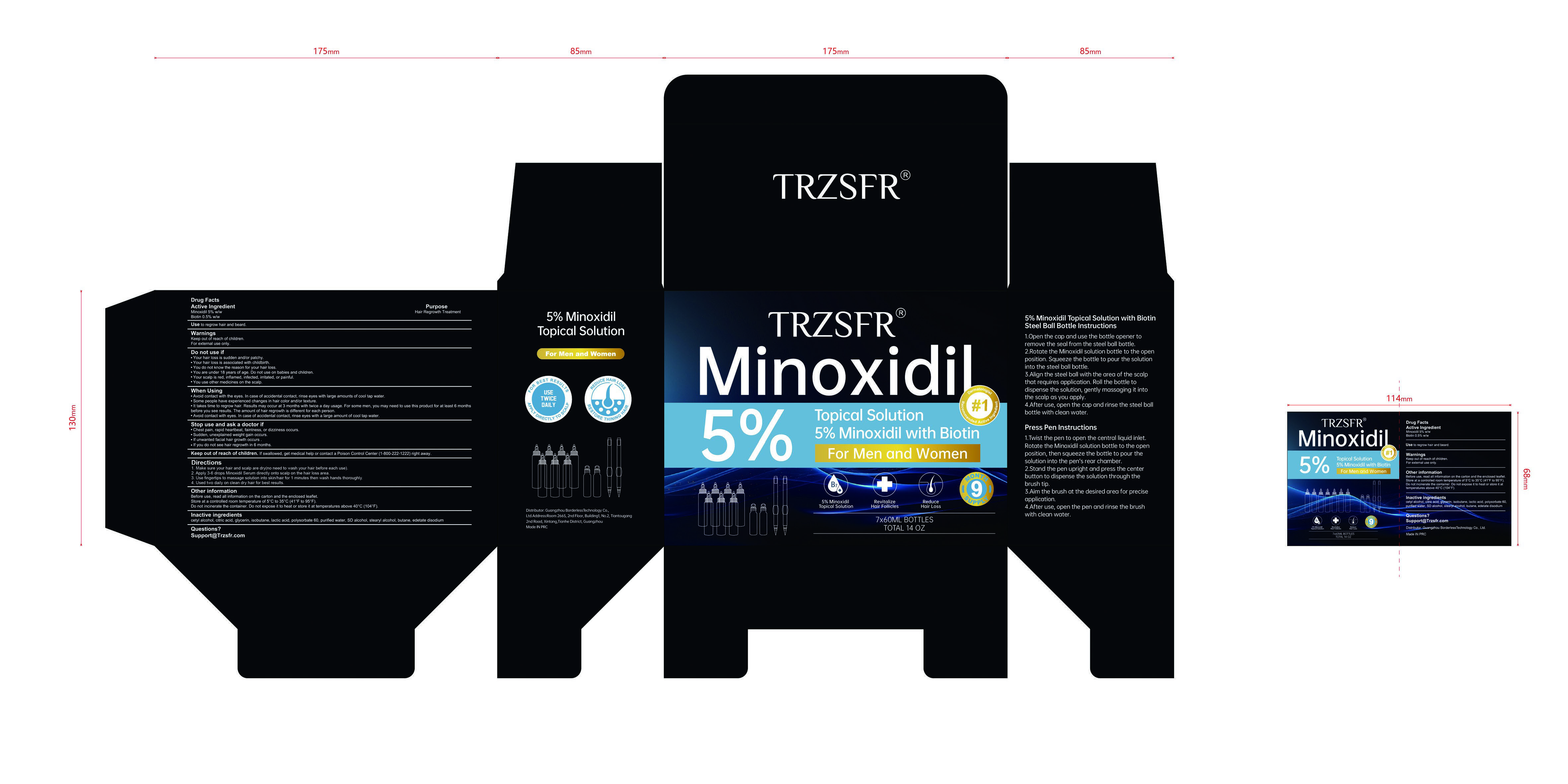 DRUG LABEL: TRZSFR 5% Minoxidil Hair Growth Sprays Serum
NDC: 85304-024 | Form: LIQUID
Manufacturer: Guangzhou Borderless Technology Co., Ltd.
Category: otc | Type: HUMAN OTC DRUG LABEL
Date: 20260202

ACTIVE INGREDIENTS: MINOXIDIL 5 g/100 mL; BIOTIN 0.5 g/100 mL
INACTIVE INGREDIENTS: ALCOHOL; DEXPANTHENOL; GLYCERIN; WATER; BUTYLENE GLYCOL; CASTOR OIL

85304-024 TRZSFR 5% Minoxidil Hair Growth Sprays Serum

ACTIVE INGREDIENT

Minoxidil 5%
Biotin 0.5%

PURPOSE

Hair Regrowth Treatment

INDICATIONS AND USAGE

Use to regrow hair and beard

Keep out of reach of children.
For external use only.

DO NOT USE

Your hair loss is sudden and/or patchy.
Your hair loss is associated with childbirth.
You do not know the reason for your hair loss.
You are under 18 years of age. Do not use on babies and children.
Your scalp is red, infamed, infected, irritated, or painful.
You use other medicines on the scalp.

WHEN USING

Avoid contact with the eyes. in case of accidental contact, rinse eyes with large amounts of cool tap water.
Some people have experienced changes in hair color and/or texture.
It takes time to regrow hair. Results may occur at 3 months with twice a day usage.For some men, you may need to use this product for at least 6 months before you see results. The amount of hair regrowth is different for each person.
Avoid contact with eyes. in case of accidental contact, rinse eyes with a large amount of cool tap water.

STOP USE

Chest pain, rapid heartbeat, faintness, or dizziness occurs.
Sudden, unexplained weight gain occurs.
lf unwanted facial hair growth occurs.
lf you do not see hair regrowth in 6 months

Keep out of reach of children. if swallowed, get medical help or contact a Poison Control Center (1-800-222-1222) right away.

DOSAGE AND ADMINISTRATION

1. ake sure your hair and scalp are dry(no need to wash your hair before each use)

2. Apply 3-6 drops Minoxidil Serum directly onto scalp on the hair loss area.

3. Use fingertips to massage solution into skin/hair for 1 minutes then wash hands thoroughly

4.Used two daily on clean dry hair for best results.

INACTIVE INGREDIENT

Butylene Glycol
Glycerin
Alcohol
Castor oil
Dexpanthenol
Water